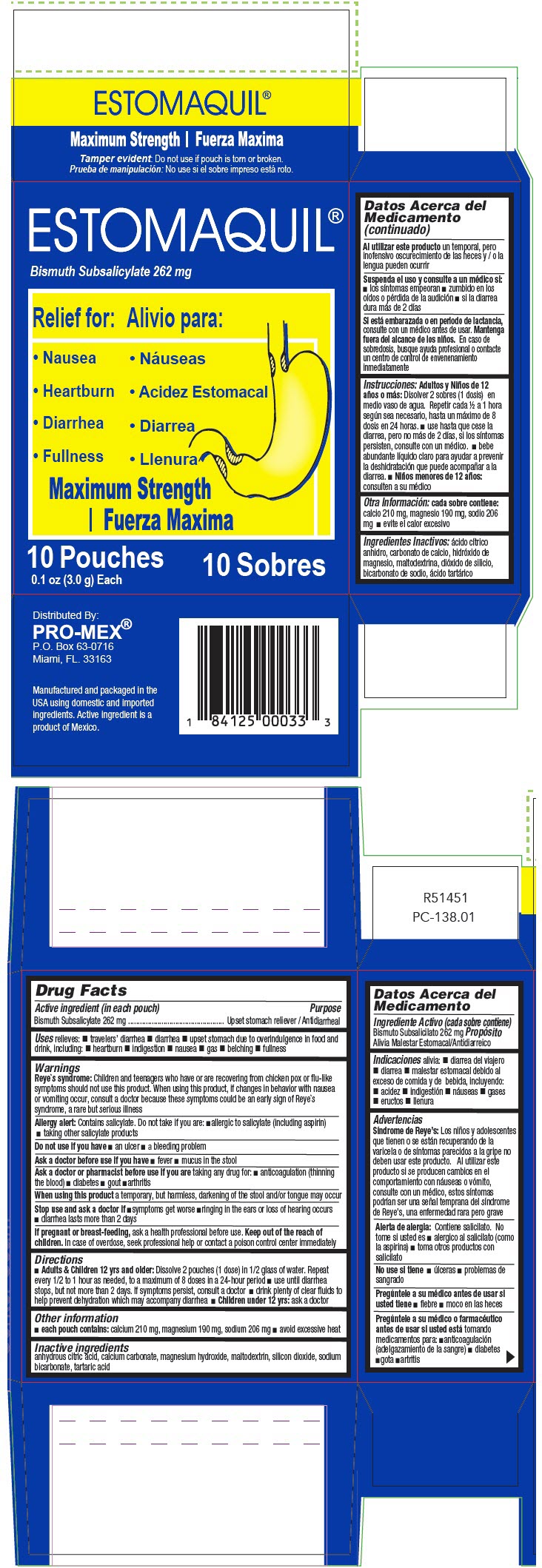 DRUG LABEL: Estomaquil Polvo
NDC: 58988-1080 | Form: POWDER
Manufacturer: ProMex LLC
Category: otc | Type: HUMAN OTC DRUG LABEL
Date: 20231129

ACTIVE INGREDIENTS: BISMUTH SUBSALICYLATE 262 mg/1 1
INACTIVE INGREDIENTS: CALCIUM CARBONATE; CITRIC ACID MONOHYDRATE; MAGNESIUM HYDROXIDE; SODIUM BICARBONATE; TARTARIC ACID; MALTODEXTRIN; SILICON DIOXIDE

Estomaquil® Polvo

Drug Facts

Active ingredient (in each pouch)

Bismuth Subsalicylate 262 mg

Purpose

Upset stomach reliever / Antidiarrheal

Uses

relieves:

- travelers' diarrhea
- diarrhea
- upset stomach due to overindulgence in food and drink, including:
  - heartburn
  - indigestion
  - nausea
  - gas
  - belching
  - fullness

Warnings

Reye`s syndrome

Children and teenagers who have or are recovering from chicken pox or flu-like symptoms should not use this product. When using this product, if changes in behavior with nausea or vomiting occur, consult a doctor because these symptoms could be an early sign of Reye`s syndrome, a rare but serious illness

Allergy alert

Contains salicylate. Do not take if you are:

- allergic to salicylate (including aspirin)
- taking other salicylate products

Do not use if you have

- an ulcer
- a bleeding problem

Ask a doctor before use if you have

- fever
- mucus in the stool

Ask a doctor or pharmacist before use if you are taking any drug for:

- anticoagulation (thinning the blood)
- diabetes
- gout
- arthritis

When using this product a temporary, but harmless, darkening of the stool and/or tongue may occur

Stop use and ask a doctor if

- symptoms get worse
- ringing in the ears or loss of hearing occurs
- diarrhea lasts more than 2 days

PREGNANCY OR BREAST FEEDING

If pregnant or breast-feeding, ask a health professional before use.

KEEP OUT OF REACH OF CHILDREN

Keep out of the reach of children. In case of overdose, seek professional help or contact a poison control center immediately

Directions

- Adults & Children 12 yrs and older: Dissolve 2 pouches (1 dose) in 1/2 glass of water. Repeat every 1/2 to 1 hour as needed, to a maximum of 8 doses in a 24-hour period
  - use until diarrhea stops, but not more than 2 days. If symptoms persist, consult a doctor
  - drink plenty of clear fluids to help prevent dehydration which may accompany diarrhea
- Children under 12 yrs: ask a doctor

Other information

- each pouch contains: calcium 210 mg, magnesium 190 mg, sodium 206 mg
- avoid excessive heat

Inactive ingredients

anhydrous citric acid, calcium carbonate, magnesium hydroxide, maltodextrin, silicon dioxide, sodium bicarbonate, tartaric acid

Distributed By:
PRO-MEX®
P.O. Box 63-0716
Miami, FL. 33163

PRINCIPAL DISPLAY PANEL - 3.0 g Pouch Carton

ESTOMAQUIL®

Bismuth Subsalicylate 262 mg

Relief for:

- Nausea
- Heartburn
- Diarrhea
- Fullness

Maximum Strength

10 Pouches
0.1 oz (3.0 g) Each